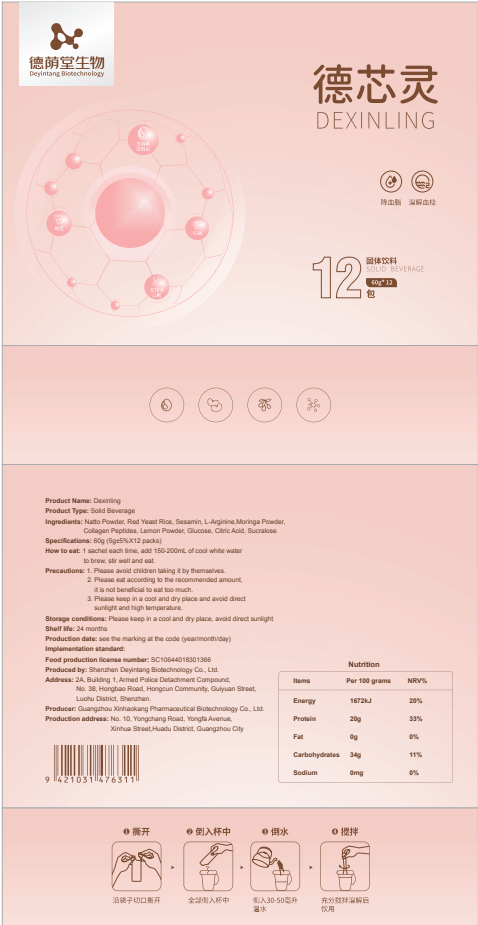 DRUG LABEL: Dexinling
NDC: 82570-005 | Form: POWDER
Manufacturer: Shenzhen Deyintang Biotechnology Co., Ltd.
Category: otc | Type: HUMAN OTC DRUG LABEL
Date: 20220221

ACTIVE INGREDIENTS: COLLAGEN, SOLUBLE, FISH SKIN 20 g/100 g; NATTOKINASE 2 g/100 g; RED YEAST 6 g/100 g; ARGININE 20 g/100 g; SESAMIN 2 g/100 g; MORINGA OLEIFERA LEAF 20 g/100 g
INACTIVE INGREDIENTS: LEMON PEEL; SUCRALOSE; CITRIC ACID MONOHYDRATE; ANHYDROUS DEXTROSE

ACTIVE INGREDIENT

Natto Powder, Red Yeast Rice, Sesamin, L-Arginine,Moringa Powder,Collagen Peptides

INACTIVE INGREDIENT

Lemon Powder, Glucose, Citric Acid, Sucralose

PURPOSE

health care

Please avoid children taking it by themselves.

How to eat

1 sachet each time, add 150-200mL of cool white water to brew,stir well and eat.

INDICATIONS AND USAGE

Please eat according to the recommended amount,it is not beneficial to eat too much.

Storage conditions

Please keep in a cool and dry place,avoid direct sunlight

WARNINGS

1. Please avoid children taking it by themselves.
2.Please eat according to the recommended amount,it is not beneficial to eat too much.
3. Please keep in a cool and dry place and avoid direct sunlight and high temperature.